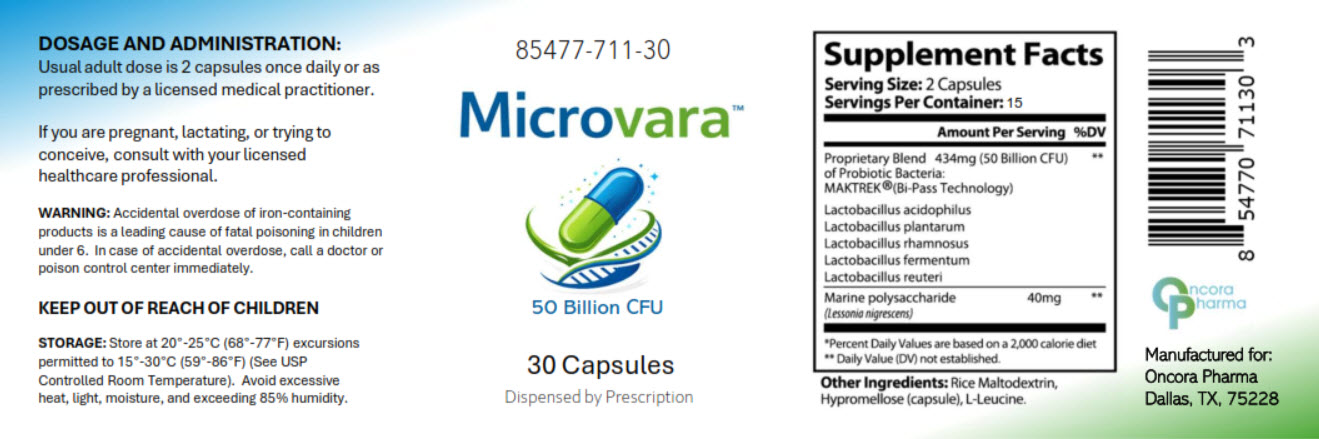 DRUG LABEL: Microvara
NDC: 85477-711 | Form: CAPSULE
Manufacturer: Oncora Pharma, LLC
Category: prescription | Type: HUMAN PRESCRIPTION DRUG LABEL
Date: 20260223

ACTIVE INGREDIENTS: LACTOBACILLUS ACIDOPHILUS 217 mg/1 1; LACTIPLANTIBACILLUS PLANTARUM 217 mg/1 1; LACTICASEIBACILLUS RHAMNOSUS 217 mg/1 1; LIMOSILACTOBACILLUS FERMENTUM 217 mg/1 1; LIMOSILACTOBACILLUS REUTERI 217 mg/1 1; LESSONIA NIGRESCENS 20 mg/1 1
INACTIVE INGREDIENTS: HYPROMELLOSE, UNSPECIFIED; MALTODEXTRIN; LEUCINE

Microvara

DESCRIPTION

Microvara™ is a prescription-dispensed oral probiotic dietary supplement formulated to support gastrointestinal health and promote balance of normal intestinal microflora. Each serving (two capsules) provides 50 billion colony-forming units (CFU) of beneficial probiotic organisms combined with marine polysaccharide.

The proprietary probiotic blend includes:

- Lactobacillus acidophilus
- Lactobacillus plantarum
- Lactobacillus rhamnosus
- Lactobacillus fermentum
- Lactobacillus reuteri

The formulation utilizes MAKTrek® Bi-Pass Technology to support probiotic viability during gastrointestinal transit.

Microvara™ is intended for use under the supervision of a licensed healthcare practitioner.

INDICATIONS AND USAGE

Microvara™ is indicated as a probiotic dietary supplement to support digestive health and maintain normal intestinal flora.

It is dispensed by prescription and intended for use under medical supervision as part of a dietary supplementation plan.

DOSAGE AND ADMINISTRATION

Adults: Take two (2) capsules once daily, or as directed by a licensed healthcare practitioner.

CONTRAINDICATIONS

Microvara™ is contraindicated in individuals with known hypersensitivity to any of its ingredients.

WARNINGS AND PRECAUTIONS

- If pregnant, nursing, or attempting to conceive, consult a licensed healthcare professional prior to use.
- Keep out of reach of children.
- Accidental overdose of iron-containing products is a leading cause of fatal poisoning in children under six years of age. In case of accidental overdose, call a physician or poison control center immediately.

ADVERSE REACTIONS

Probiotic supplementation may occasionally result in mild gastrointestinal symptoms such as bloating, gas, or abdominal discomfort. If adverse reactions occur, discontinue use and consult a healthcare professional.

HOW SUPPLIED

Microvara™ (NDC 85477-711-30) is supplied in bottles containing 30 capsules.

STORAGE

Store at 20°–25°C (68°–77°F); excursions permitted to 15°–30°C (59°–86°F).
Protect from excessive heat, moisture, and light.